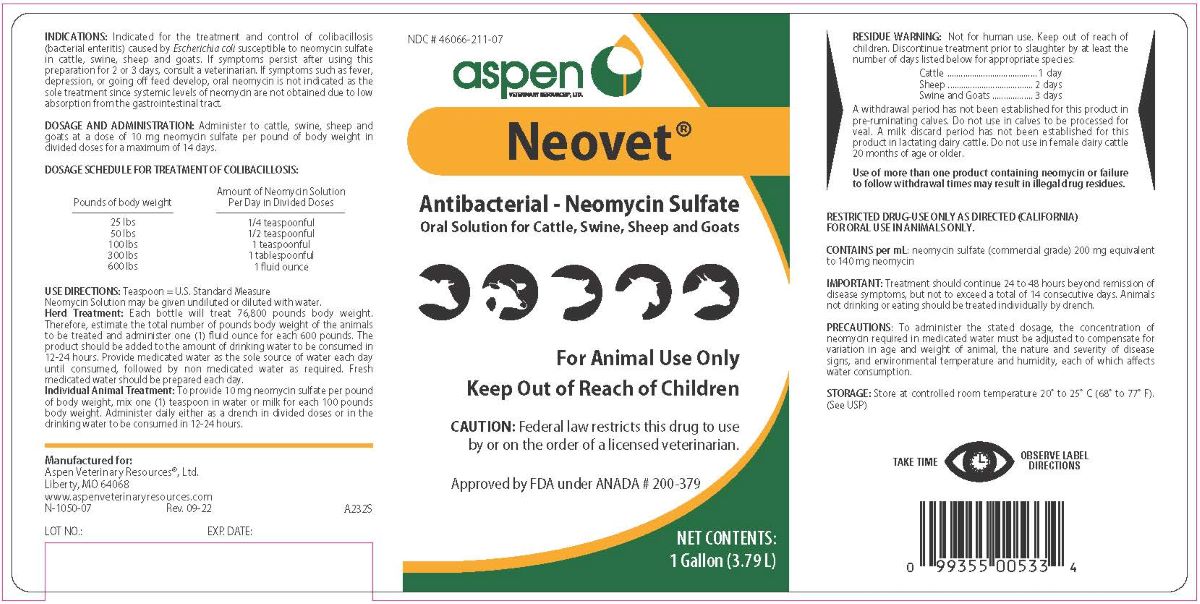 DRUG LABEL: Neovet
NDC: 46066-211 | Form: LIQUID
Manufacturer: Aspen Veterinary Resources, Ltd.
Category: animal | Type: PRESCRIPTION ANIMAL DRUG LABEL
Date: 20240426

ACTIVE INGREDIENTS: NEOMYCIN SULFATE 140 mg/1 mL
INACTIVE INGREDIENTS: METHYLPARABEN; POTASSIUM SORBATE; PROPYLPARABEN; SODIUM CITRATE; SODIUM METABISULFITE; WATER

Neovet

INDICATIONS AND USAGE

Antibacterial - Neomycin Sulfate

Oral Solution for Cattle, Swine, Sheep and Goats

For Animal Use Only

Keep Out of Reach of Children

CAUTION: Federal law restricts this drug to use by or on the order of a licensed veterinarian.

Approved by FDA under ANADA # 200-379

INDICATIONS: Indicated for the treatment and control of colibacillosis (bacterial enteritis) caused by Escherichia coli susceptible to neomycin sulfate in cattle, swine, sheep and goats. If symptoms persist after using this preparation for 2 or 3 days, consult a veterinarian. If symptoms such as fever, depression, or going off feed develop, oral neomycin is not indicated as the sole treatment since systemic levels of neomycin are not obtained due to low absorption from the gastrointestinal tract.

DOSAGE AND ADMINISTRATION

Administer to cattle, swine, sheep and goats at a dose of 10 mg neomycin sulfate per pound of body weight in divided doses for a maximum of 14 days.

DOSAGE SCHEDULE FOR TREATMENT OF COLIBACILLOSIS:

Amount of Neomycin Solution
Pounds of body weight Per Day in Divided Doses

25 lbs 1/4 teaspoonful

50 lbs 1/2 teaspoonful

100 lbs 1 teaspoonful

300 lbs 1 tablespoonful

600 lbs 1 fluid ounce

USE DIRECTION: Teaspoon = U.S. Standard Measure

Neomycin Solution may be given undiluted or diluted with water.

Herd Treatment: Each bottle will treat 76,800 pounds body weight. Therefore, estimate the total number of pounds body weight of the animals to be treate3d and administer one (1) fluid ounce for each 600 pounds. The product should be added to the amount of drinking water to be consumed in 12-24 hours. Provide medicated water as the sole source of water each day until consumed, followed by non-medicated water as required. Fresh medicated water should be prepared each day.

Individual Animal Treatment: To provide 10 mg neomycin sulfate per pound of body weight, mix one (1) teaspoon in water or milk for each 100 pounds body weight. Administer daily either as a drench in divided doses or in the drinking water to consumed in 12-24 hours.

RESIDUE WARNING

Not for human use. Keep out of reach of children. Discontinue treatment prior to slaughter by at least the number of days listed below for appropriate species:

Cattle 1 day

Sheep 2 days

Swine and Goats 3 days

A withdrawal period has not been established for this product in pre-ruminating calves. Do not use in calves to be processed for veal. A milk discard period has not been established for this product in lactating dairy cattle. Do not use in female dairy cattle 20 months or age or older.

Use of more than one product containing neomycin or failure to sollow withdrawal times may result in illegal drug residues.

RESTRICTED DRUG-USE ONLY AS DIRECTED (CALIFORNIA) FOR ORAL USE IN ANIMALS ONLY.

CONTAINS per mL:

neomycin sulfate (commercial grade) 200 mg equivalent to 140 mg neomycin.

IMPORTANT: Treatment should continue 24 to 48 hours beyond remission of disease symptoms, but not to exceed to total of 14 consecutive days. Animals not drinking or eating should be treated individually by drench.

PRECAUTIONS

To administer the stated dosage, the concentration of neomycin required in medicated water must be adjusted to compensate for variation in age and weight of animal, the nature and severity of disease signs, and environmental temperature and humidity, each of which affects water consumption.

STORAGE

Store at controlled room temperature 20° to 25°C (68° to 77°F). (See USP)